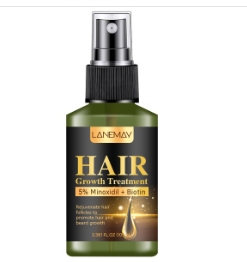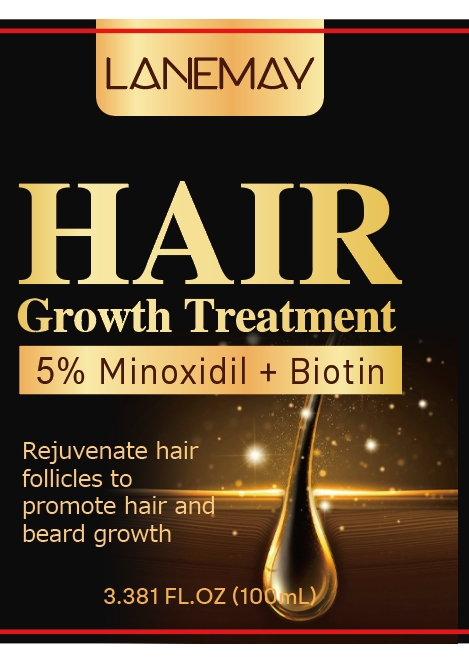 DRUG LABEL: Hair Growth Treatment
NDC: 84025-064 | Form: LIQUID
Manufacturer: Guangzhou Yanxi Biotechnology Co., Ltd
Category: otc | Type: HUMAN OTC DRUG LABEL
Date: 20240711

ACTIVE INGREDIENTS: MINOXIDIL 5 g/100 mL; PROPANEDIOL 2 g/100 mL
INACTIVE INGREDIENTS: WATER

DOSAGE AND ADMINISTRATION

Use as a common essential oil

WARNINGS

Keep out of Children

INACTIVE INGREDIENT

Aqua

INDICATIONS AND USAGE

Use as a common essential oil

Keep out of Children

PURPOSE

It can make your hair growmore.